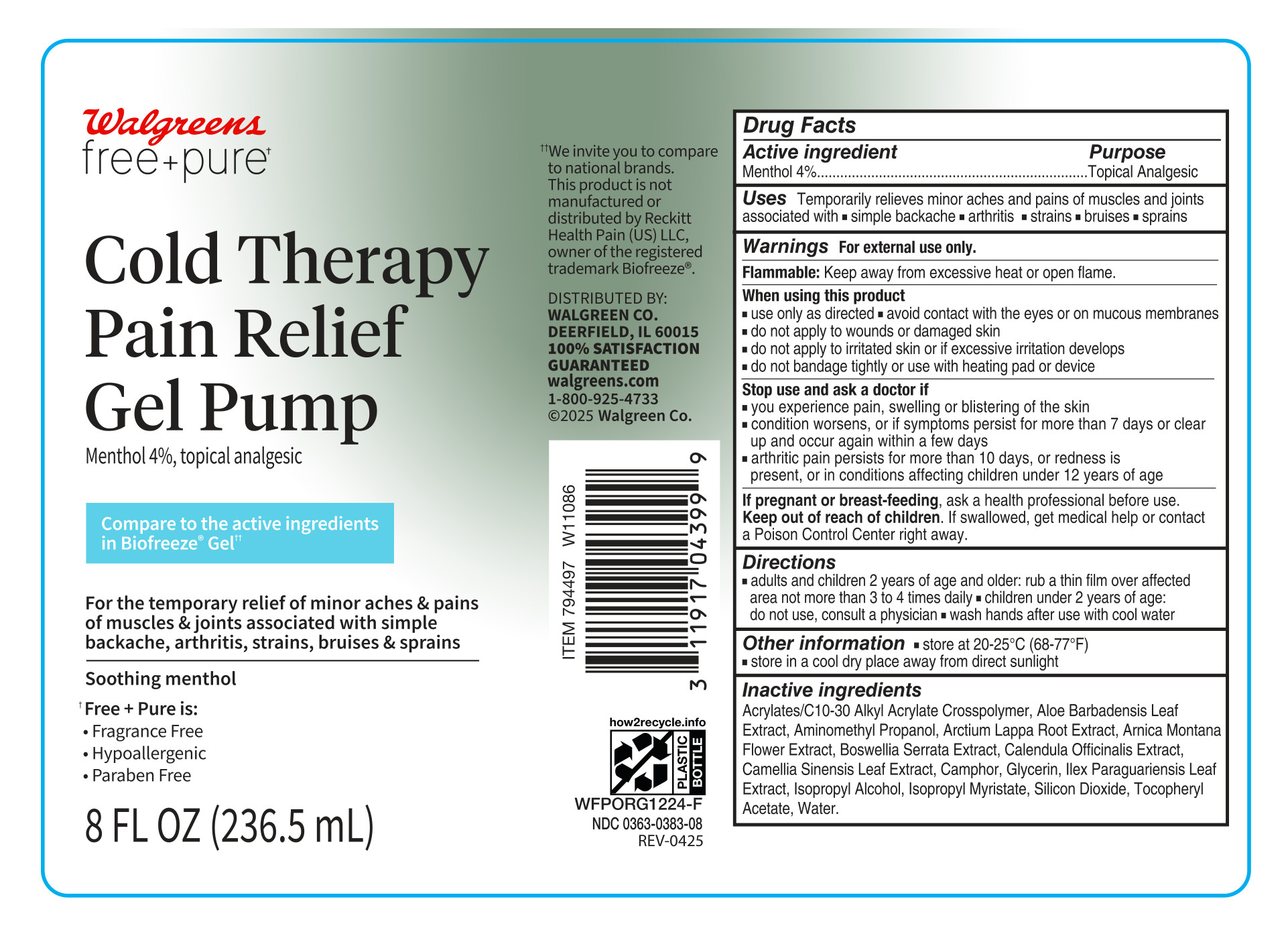 DRUG LABEL: Free and Pure Cold Therapy Pain Relief
NDC: 0363-0383 | Form: GEL
Manufacturer: Walgreen Co.
Category: otc | Type: HUMAN OTC DRUG LABEL
Date: 20250612

ACTIVE INGREDIENTS: MENTHOL, UNSPECIFIED FORM 36 mg/1 mL
INACTIVE INGREDIENTS: ARCTIUM LAPPA ROOT; ARNICA MONTANA FLOWER; INDIAN FRANKINCENSE; ILEX PARAGUARIENSIS LEAF; WATER; CAMPHOR (SYNTHETIC); GLYCERIN; SILICON DIOXIDE; .ALPHA.-TOCOPHEROL ACETATE, DL-; MEDIUM-CHAIN TRIGLYCERIDES; AMINOMETHYL PROPANOL; ACRYLATES/C10-30 ALKYL ACRYLATE CROSSPOLYMER (60000 MPA.S); GREEN TEA LEAF; ALOE VERA LEAF; CALENDULA OFFICINALIS FLOWER; ISOPROPYL ALCOHOL; ISOPROPYL MYRISTATE

Free and Pure Cold Therapy Pain Relief

Active ingredient

Menthol 4%

Purpose

Topical analgesic

Uses

Temporarily relieves minor aches and pains of muscles and joing associated with

- simple backache
- arthritis
- strains
- bruises
- sprains

Warnings

For external use only.

Flammable: Keep away from excessive heat or open flame.

When using this product

- use only as directed
- avoid contact with the yes or on mucous membranes
- do not apply to wounds or damaged skin
- do not apply to irritate skin or if excessive irritation develops
- do not bandage tightly or use with heating pad or device

Stop use and ask a doctor if

- you experience pain, swelling, or blistering of the skin
- condition worsens, or if symptoms persist for more than 7 days or clear up and occur again within a few days
- arthritic pain persists for more than 10 days, or redness is present, or in conditions affecting children under 12 years of age

If pregnant or breast-feeding

ask a health professional before use

Keep out of reach of children

If swallowed, get medical help or contact a Poison Control Center right away

Directions

- adults and children 2 years of age and older: rub a thin film over affected area not more than 3 to 4 times daily
- children under 2 years of age: do not use, consult a physician
- wash hands after use with cool water

Other information

- store at 20-25°C (68-77°F)
- store in a cool dry place away from direct sunlight

Inactive ingredients

Acrylates/C10-30 Alkyl Acrylate Crosspolymer, Aloe Barbadensis Leaf Extract, Aminomethyl Propanol, Arctium Lappa Root Extract, Arnica Montana Flower Extract, Boswellia Serrata Extract, Calendula Officinalis Extract, Camellia Sinensis Leaf Extract, Camphor, Glycerin, Ilex Paraguariensis Leaf Extract, Isopropyl Alcohol, Isopropyl Myristate, Silicon Dioxide, Tocopheryl Acetate, Water

Principal Display Panel - 8 fl oz

Walgreens Free and Puret

Cold Therapy Pain Relief Gel Pump

Menthol 4%, topical analgesic

Compare to the active ingredient in Biofreeze® Geltt

For the temporary relief of minor aches & pains of muscles & joints associated with simple backache, arthritis, strains, bruises & sprains

Soothing menthol

tFree + Pure is:

- Fragrance Free
- Hypoallergenic
- Paraben Free

8 FL OZ (236.5 mL)